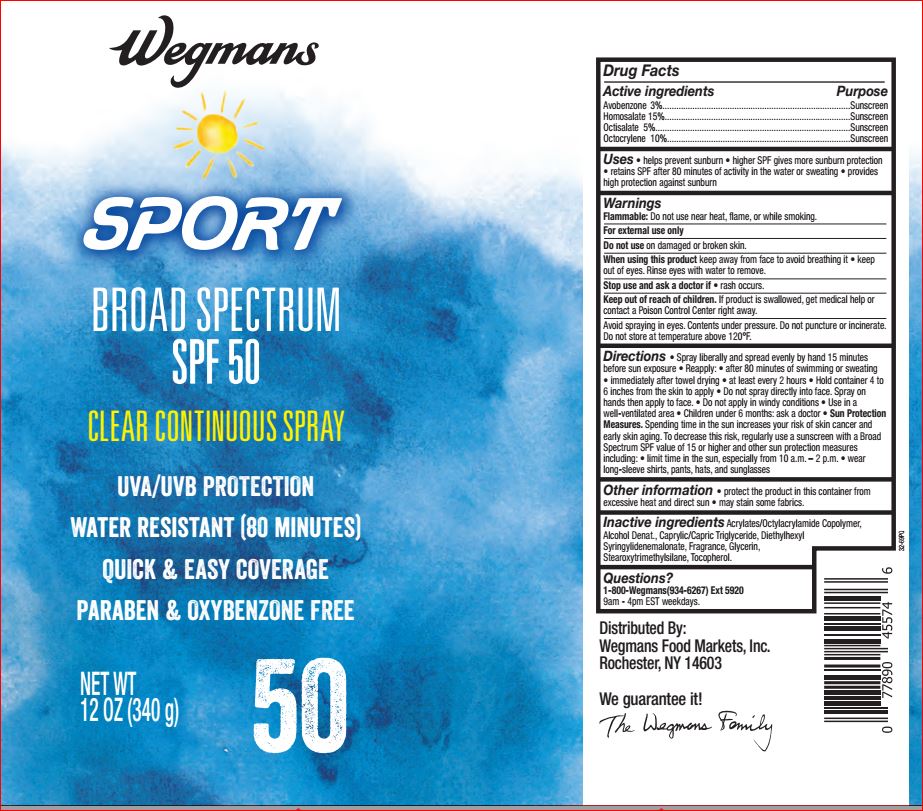 DRUG LABEL: Sport Sunscreen SPF 50
NDC: 47124-118 | Form: SPRAY
Manufacturer: Wegman
Category: otc | Type: HUMAN OTC DRUG LABEL
Date: 20180709

ACTIVE INGREDIENTS: Avobenzone 3.0 1/100 g; Homosalate 15.0 1/100 g; Octisalate 5.0 1/100 g; Octocrylene 10.0 1/100 g
INACTIVE INGREDIENTS: ALCOHOL; MEDIUM-CHAIN TRIGLYCERIDES; Diethylhexyl Syringylidenemalonate; Glycerin; Stearoxytrimethylsilane; Tocopherol

Active ingredients Purpose

Avobenzone 3%..................................................................................Sunscreen
Homosalate 15%.................................................................................Sunscreen
Octisalate 5%......................................................................................Sunscreen
Octocrylene 10%.................................................................................Sunscreen

INDICATIONS AND USAGE

Uses • helps prevent sunburn • higher SPF gives more sunburn protection
• retains SPF after 80 minutes of activity in the water or sweating • provides
high protection against sunburn

Warnings For external use only

Flammable: Do not use near heat, flme, or while smoking.
Do not use on damaged or broken skin
When using this product • Keep out of eyes. Rinse eyes with water to remove.
Stop use and ask a doctor if rash occurs
Keep out of reach of children. If product is swallowed, get medical help or
contact a Poison Control Center right away.

DOSAGE AND ADMINISTRATION

Directions • spray liberally and spread evenly by hand 15 minutes before sun
exposure • reapply: • after 80 minutes of swimming or sweating • immediately after
towel drying • at least every 2 hours • hold container 4 to 6 inches from the skin to apply
• do not spray directly into face. Spray on hands then apply to face. • do not apply in
windy conditions • use in a well-ventilated area
• Sun Protection Measures. Spending time in the sun increases your risk of skin cancer and
early skin aging. To decrease this risk, regularly use a sunscreen with a broad spectrum SPF of
15 or higher and other sun protection measures including: • limit time
in the sun, especially from 10 a.m. - 2 p.m. • wear long-sleeve shirts,
pants, hats, and sunglasses
• children under 6 months: Ask a doctor

INACTIVE INGREDIENT

Inactive ingredients: Acrylates/Octylacrylamide, Copolymer, Alcohol Denat., Caprylic/Capric Triglyceride, Diethylhexyl Syringylidenemalonate, Fragrance, Glycerin, Stearoxytrimethylsilane, Tocopherol.

Questions?
1-800-Wegmans(934-6267) Ext 5920
9am - 4pm EST weekdays